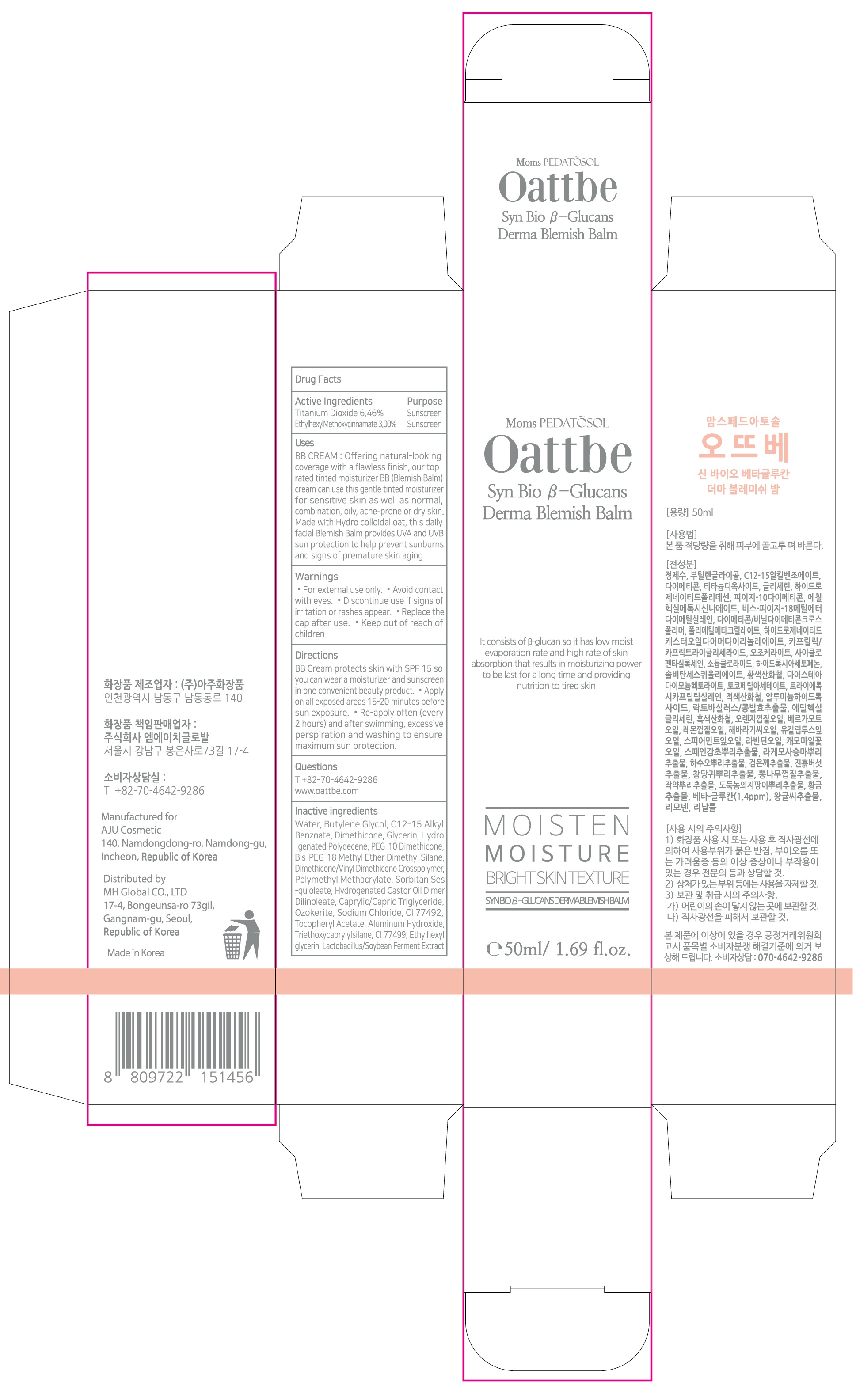 DRUG LABEL: PEDATOSOL OATTBE SYN BIO BETA GLUCANS DERMA BLEMISH BALM
NDC: 73113-050 | Form: CREAM
Manufacturer: Mh Global Co., Ltd.
Category: otc | Type: HUMAN OTC DRUG LABEL
Date: 20210108

ACTIVE INGREDIENTS: Titanium Dioxide 3.23 g/50 mL; OCTINOXATE 1.50 g/50 mL
INACTIVE INGREDIENTS: Water; Butylene Glycol; ALKYL (C12-15) BENZOATE; Dimethicone

ACTIVE INGREDIENTS

Titanium Dioxide 6.46%
Ethylhexyl Methoxycinnamate 3.00%

INACTIVE INGREDIENTS

Water, Butylene Glycol, C12-15 Alkyl Benzoate, Dimethicone, Glycerin, Hydrogenated Polydecene, PEG-10 Dimethicone, Bis-PEG-18 Methyl Ether Dimethyl Silane, Dimethicone/Vinyl Dimethicone Crosspolymer, Polymethyl Methacrylate, Sorbitan Sesquioleate, Hydrogenated Castor Oil Dimer Dilinoleate, Caprylic/Capric Triglyceride, Ozokerite, Sodium Chloride, CI 77492, Tocopheryl Acetate, Aluminum Hydroxide, Triethoxycaprylylsilane, CI 77499, Ethylhexylglycerin, Lactobacillus/Soybean Ferment Extract

PURPOSE

Sunscreen

WARNINGS

For external use only. Avoid contact with eyes. Discontinue use if signs of irritation or rashes appear. Replace the cap after use. Keep out of reach of children

KEEP OUT OF REACH OF CHILDREN

Uses

BB CREAM : Offering natural-looking coverage with a flawless finish, our top-rated tinted moisturizer BB (Blemish Balm) cream can use this gentle tinted moisturizer for sensitive skin as well as normal, combination, oily, acne-prone or dry skin. Made with Hydro colloidal oat, this daily facial Blemish Balm provides UVA and UVB sun protection to help prevent sunburns and signs of premature skin aging

Directions

BB Cream protects skin with SPF 15 so you can wear a moisturizer and sunscreen in one convenient beauty product. ■ Apply on all exposed areas 15-20 minutes before sun exposure. ■ Re-apply often (every 2 hours) and after swimming, excessive perspiration and washing to ensure maximum sun protection.

QUESTIONS

T +82-70-4642-9286

www.oattbe.com